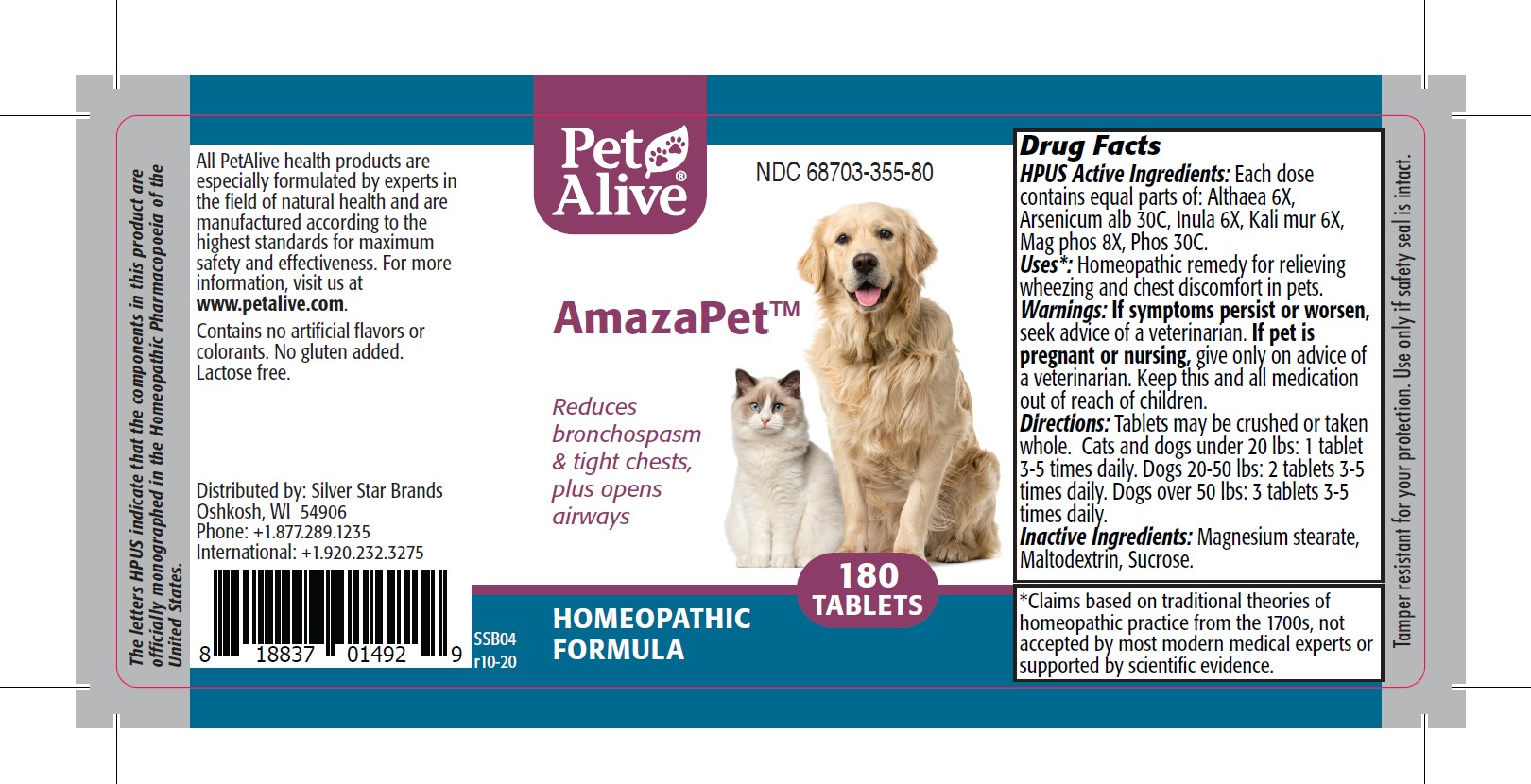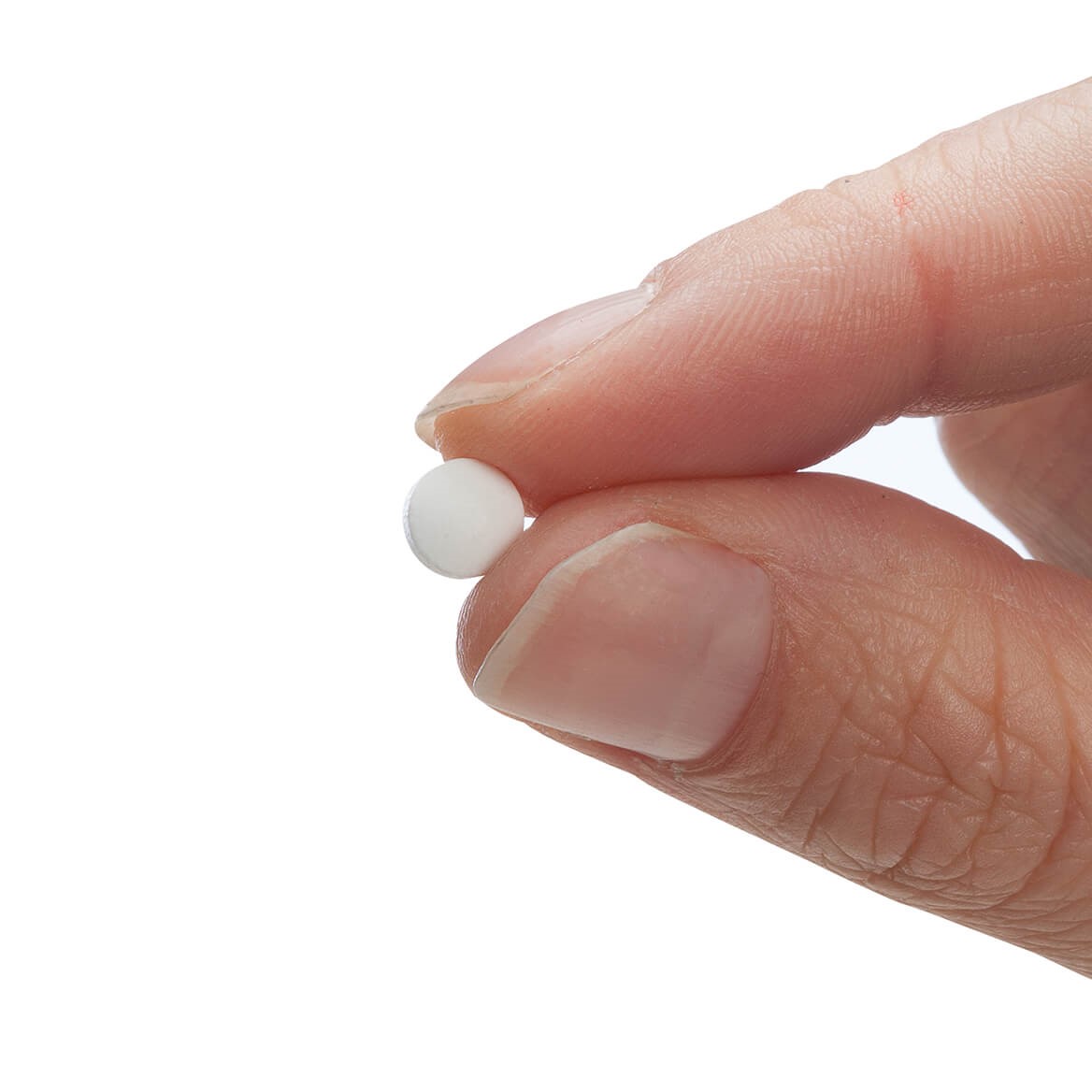 DRUG LABEL: AmazaPet
NDC: 68703-355 | Form: TABLET
Manufacturer: SILVER STAR BRANDS
Category: homeopathic | Type: HUMAN OTC DRUG LABEL
Date: 20251212

ACTIVE INGREDIENTS: POTASSIUM CHLORIDE 6 [hp_X]/180 1; MAGNESIUM PHOSPHATE, DIBASIC TRIHYDRATE 8 [hp_X]/180 1; ARSENIC TRIOXIDE 30 [hp_C]/180 1; INULA HELENIUM WHOLE 6 [hp_X]/180 1; ALTHAEA OFFICINALIS LEAF 6 [hp_X]/180 1; PHOSPHORUS 30 [hp_C]/180 1
INACTIVE INGREDIENTS: SUCROSE; MAGNESIUM STEARATE; MALTODEXTRIN

PetAlive® AmazaPet™ Tablets

HPUS Active Ingredient

HPUS Active Ingredients: Each dose contains equal parts of: Althaea 6X, Arsenicum alb 30C, Inula 6X, Kalu mur 6X, Mag phos 8X, Phos 30C.

Uses*

Uses*: Homeopathic remedy for relieving wheezing and chest discomfort in pets.

Warnings

Warnings: If symptoms persist or worsen, seek advice of a veterinarian. If pet is pregnant or nursing, give only on advice of a veterinarian. Keep thi and all medicaiton out of reach of children.

Directions

Directions: Tablets may be crushed or taken whole. Cats and dogs under 20lbs: 1 tablet 3-5 times daily. Dogs 20-50lbs: 2tablets 3-5 times daily. Dogs over 50lbs: 3 tablets 3-5 times daily.

OTHER SAFETY INFORMATION

Tamper resistant for your protection. Use only if safety seal is intact.

Contins no artificial flavors or colorants. No gluten added. Lactose free.

Inactive Ingredients

Inactive Ingredients: Magnesium stearate, Maltodextrin, Sucrose

KEEP OUT OF REACH OF CHILDREN

Keep this and all medication out of reach of children.

PREGNANCY OR BREAST FEEDING

If pet is pregnant or nursing, give only on advice of a veterinarian.

PURPOSE

Reduces bronchospasm & tight chests, plus open airways